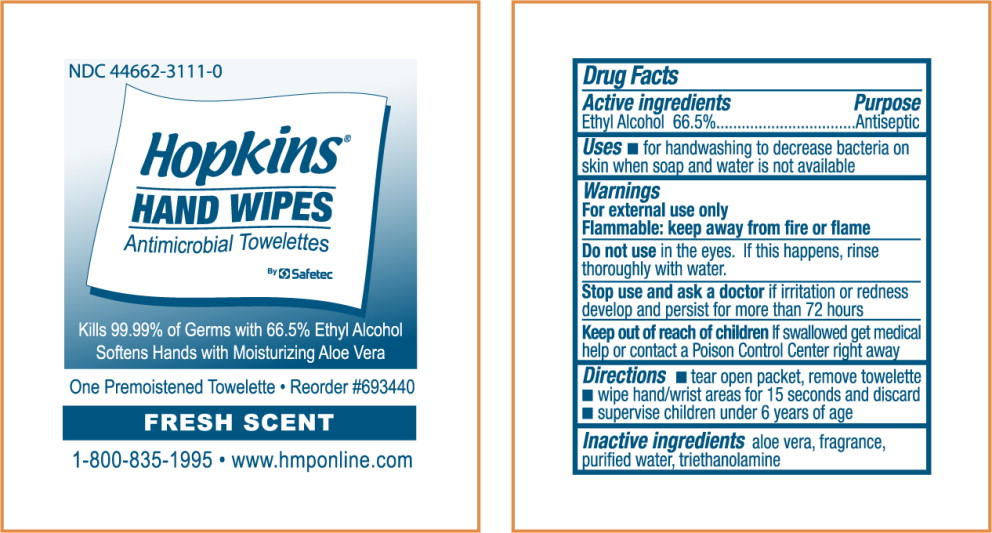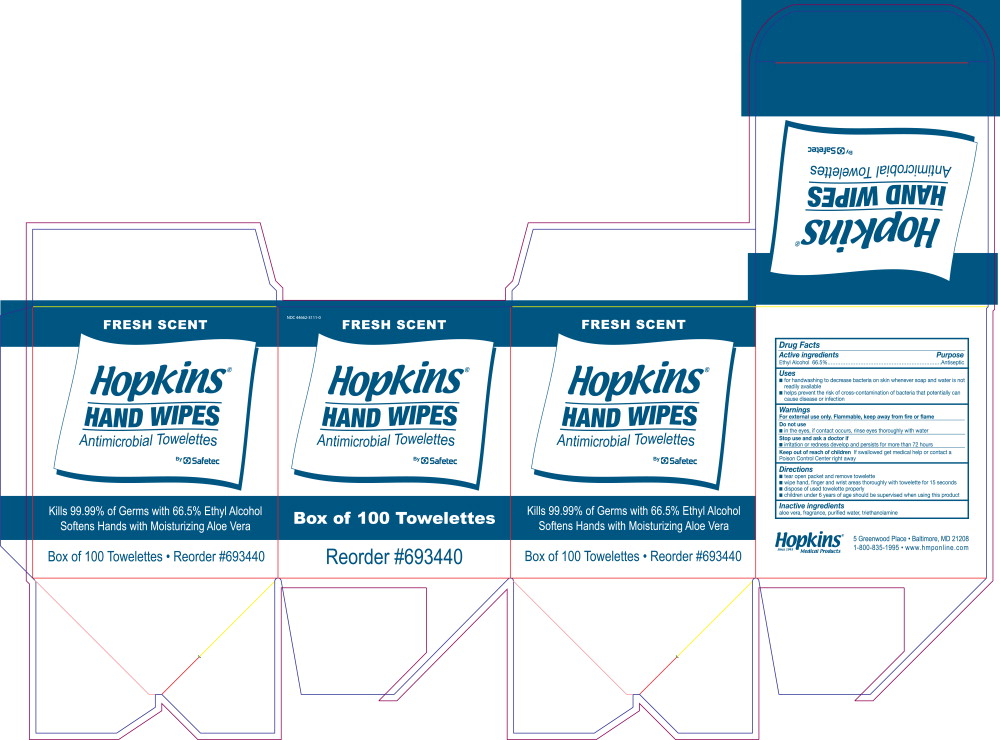 DRUG LABEL: Antimicrobial
NDC: 44662-3111 | Form: LIQUID
Manufacturer: Hopkins Medical
Category: otc | Type: HUMAN OTC DRUG LABEL
Date: 20131030

ACTIVE INGREDIENTS: alcohol 700 mL/1 L
INACTIVE INGREDIENTS: aloe; water; trolamine

HOPKINS
ANTIMICROBIAL TOWELETTES

Drug Facts

Active Ingredients

Ethyl Alcohol 66.5%

Purpose

Antiseptic

Uses

- for handwashing to decrease bacteria on skin whenever soap and water is not readily available
- helps prevent the risk of cross-contamination of bacteria that potentially can cause disease or infection

Warnings

For external use only. Flammable, keep away from fire or flame

Do not use

- in the eyes, if contact occurs, rinse eyes thoroughly with water.

Stop use and ask doctor if

- irritation or redness develop and persist for more than 72 hours

Keep out of reach of children If swallowed get medical help or contact a Poison Control Center right away

Directions

- tear open packet, remove towelette
- wipe hand, finger and wrist areas thoroughly with towelette for 15 seconds
- dispose of used towelette properly
- children under 6 years of age should be supervised when using this product

Inactive ingredients

aloe vera, fragrance, purified water, triethanolamine

PRINCIPAL DISPLAY PANEL – Antimicrobial Skin Wipe packet

NDC 44662-3111-0

Hopkins
HAND WIPES
Antimicrobial Towelettes
By Safetec

Kills 99.99% of Germs with 66.5% Ethyl Alcohol
Softens Hands with Moisturizing Aloe Vera

One Premoistened Towelette • Reorder #693440
FRESH SCENT

1-800-835-1995 • www.hmponline.com

PRINCIPAL DISPLAY PANEL – Antimicrobial Skin Wipe box

NDC 44662-3111-0

FRESH SCENT

Hopkins
HAND WIPES
Antimicrobial Towelettes
By Safetec

Box of 100 Towelettes
Reorder #693440